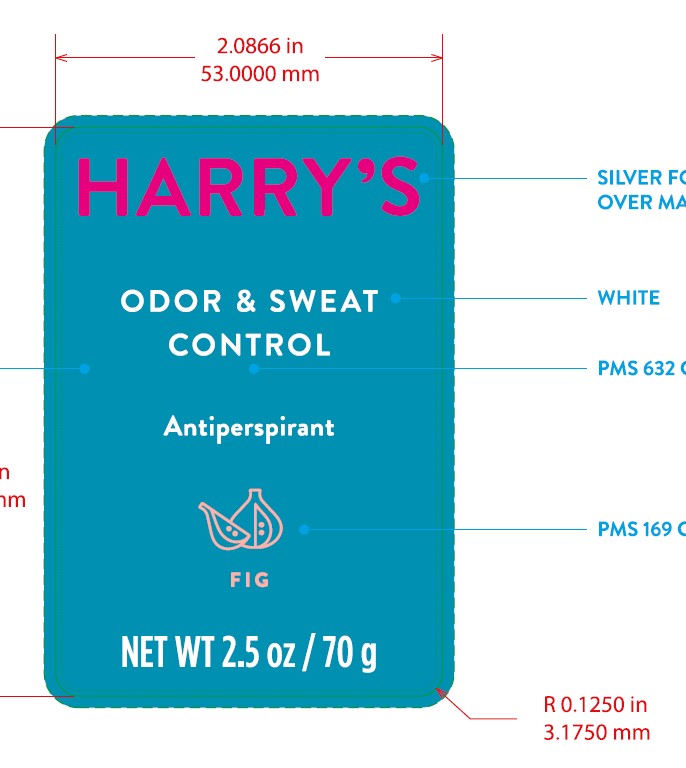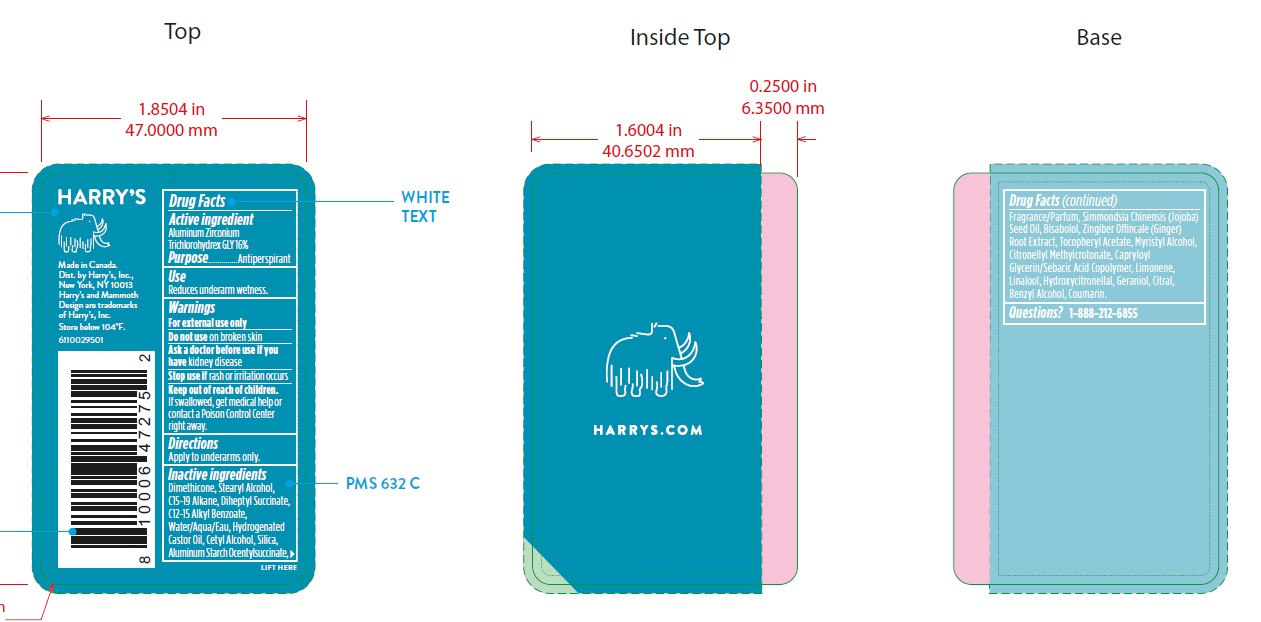 DRUG LABEL: Harrys Antiperspirant Fig
NDC: 70533-007 | Form: STICK
Manufacturer: Harry's Inc.
Category: otc | Type: HUMAN OTC DRUG LABEL
Date: 20221222

ACTIVE INGREDIENTS: ALUMINUM ZIRCONIUM TRICHLOROHYDREX GLY 160 mg/1 g
INACTIVE INGREDIENTS: FRAGRANCE 13576; DIHEPTYL SUCCINATE; .ALPHA.-BISABOLOL, (+/-)-; COUMARIN; HYDROGENATED CASTOR OIL; GINGER; .ALPHA.-TOCOPHEROL ACETATE; MYRISTYL ALCOHOL; CITRONELLYL METHYLCROTONATE; HYDROXYCITRONELLAL; SILICON DIOXIDE; JOJOBA OIL; LIMONENE, (+/-)-; GERANIOL; ALKYL (C12-15) BENZOATE; WATER; ALUMINUM STARCH OCTENYLSUCCINATE; CITRAL; DIMETHICONE; CETYL ALCOHOL; LINALOOL, (+/-)-; BENZYL ALCOHOL; STEARYL ALCOHOL; CAPRYLOYL GLYCERIN/SEBACIC ACID COPOLYMER (2000 MPA.S)

AP - Fig

Active Ingredient

ALUMINUM ZIRCONIIUM TRICHLOROHYDREX GLY 16%

Purpose

Antiperspirant

Use

Reduces underarm wetness

Warnings

For external Use only

Do not use on broken skin

Ask doctor before use if you have kidney disease

Stop use if rash or irritation occurs.

Keep out of reach of children. If swallowed, get medical help or contact a Poison Control Center right away.

Directions

Apply to underarms only

Inactive Ingredients

DIMETHICONE, STEARYL ALCOHOL, C15-19 ALKANE, DIHEPTYL SUCCINATE, C12-15 ALKYL BENZOATE, WATER/AQUA/EAU, HYDROGENATED CASTOR OIL, CETYL ALCOHOL, SILICA, ALUMINUM STARCH OCENTYLSUCCINATE, FRAGRANCE/PARFUM, SIMMONDSIA CHINENSIS (JOJOBA) SEED OIL, BISABOLOL, ZINGIBER OFFINCALE (GINGER) ROOT EXTRACT, TOCOPHERYL ACETATE, MYRISTYL ALCOHOL, CITRONELLYL METHYLCROTONATE, CAPRYLOYL GLYCERIN/SEBACIC ACID COPOLYMER, LIMONENE, LINALOOL, HYDROXYCITRONELLAL, GERANIOL, CITRAL, BENZYL ALCOHOL, COUMARIN.

Questions?: 1-888-212-6855

PACKAGE LABEL

NDC 70533-007-25